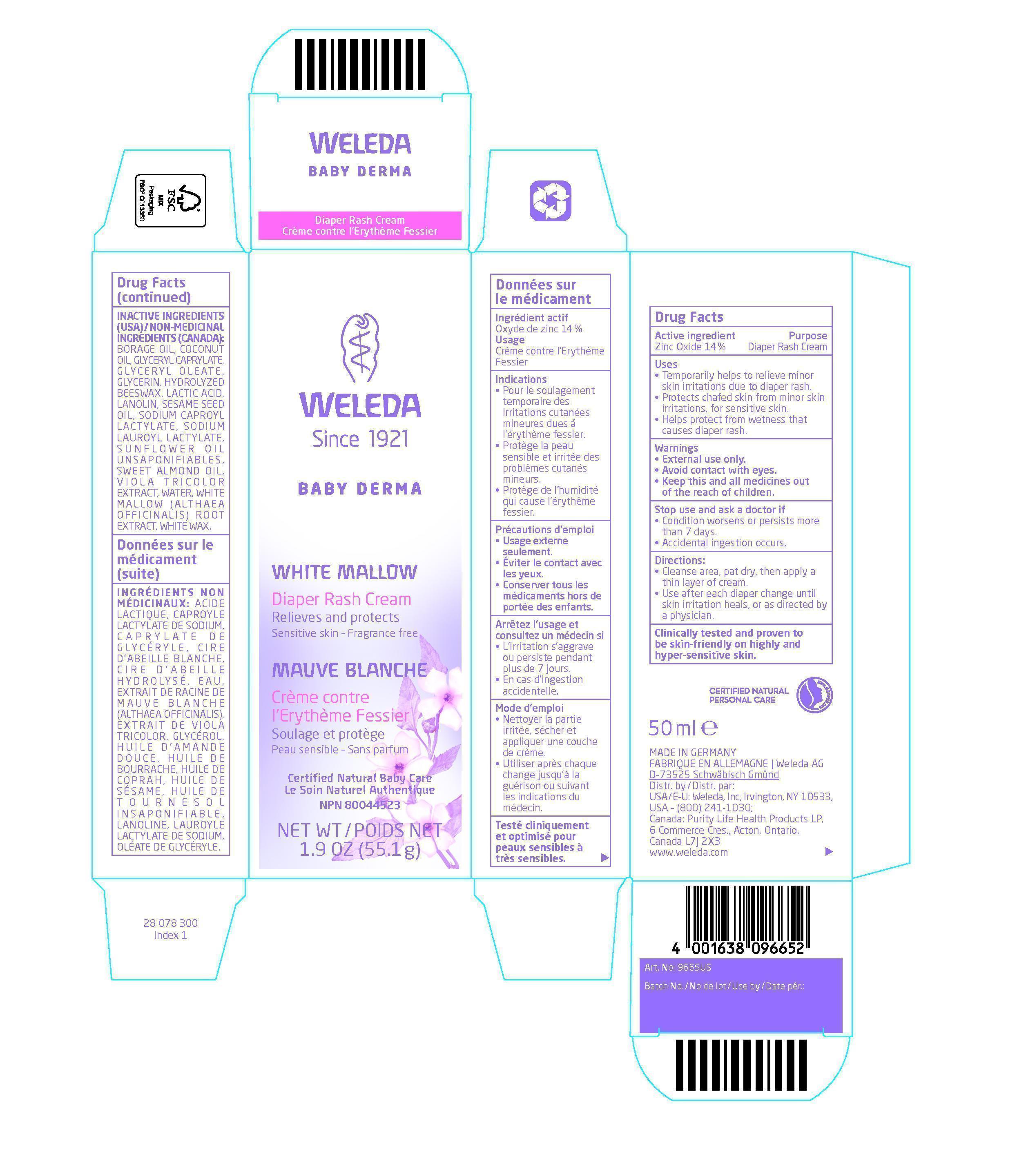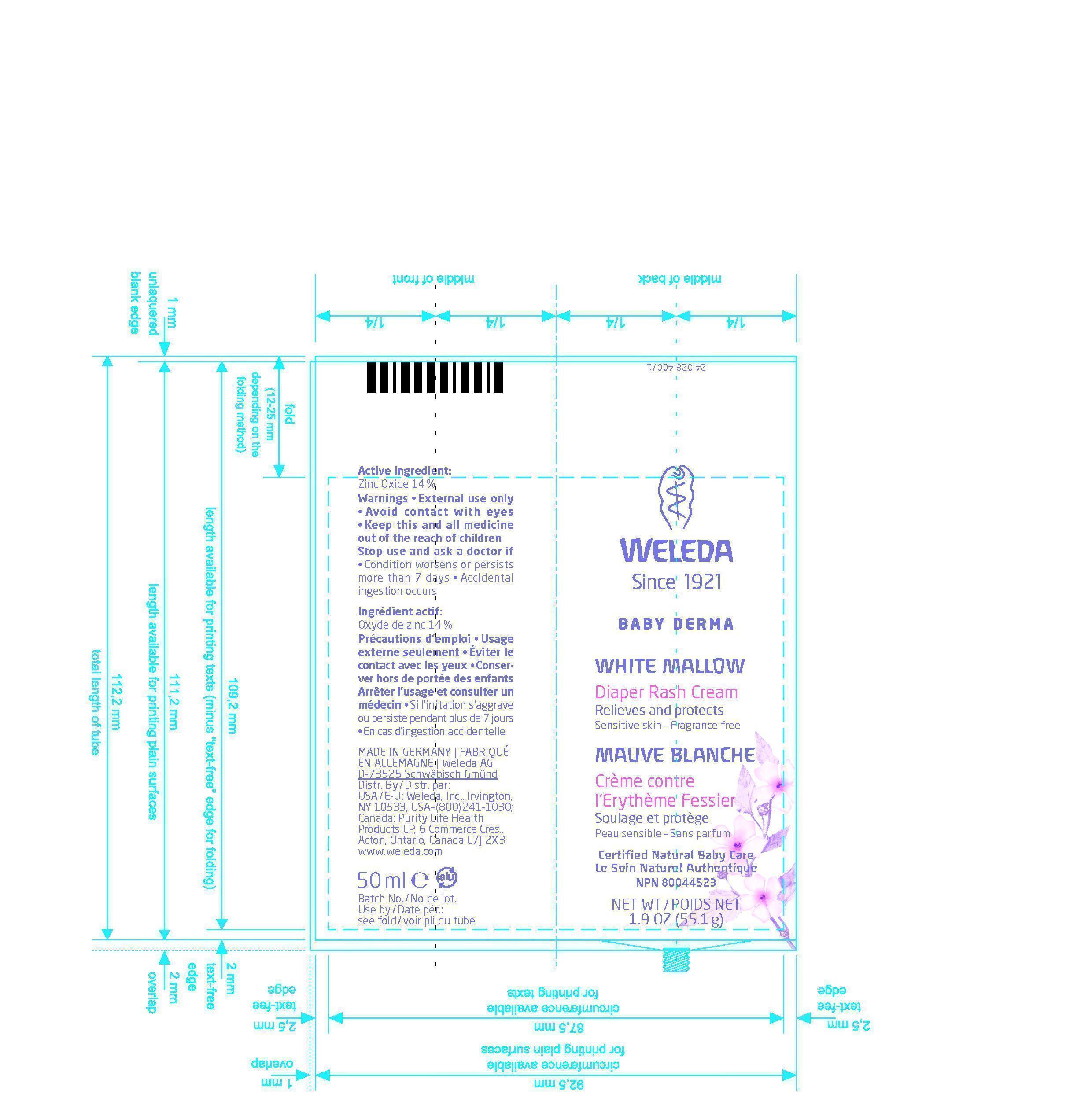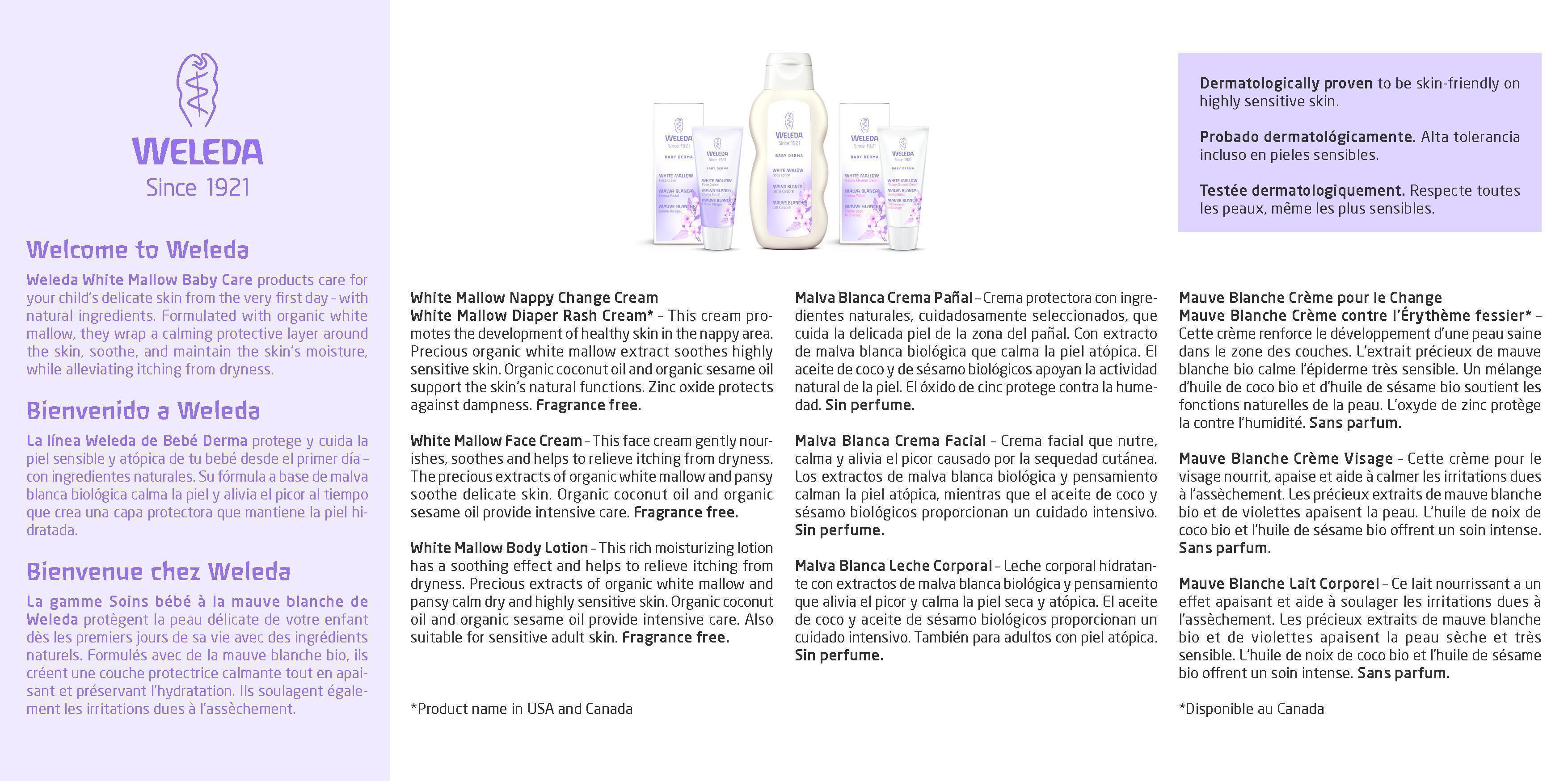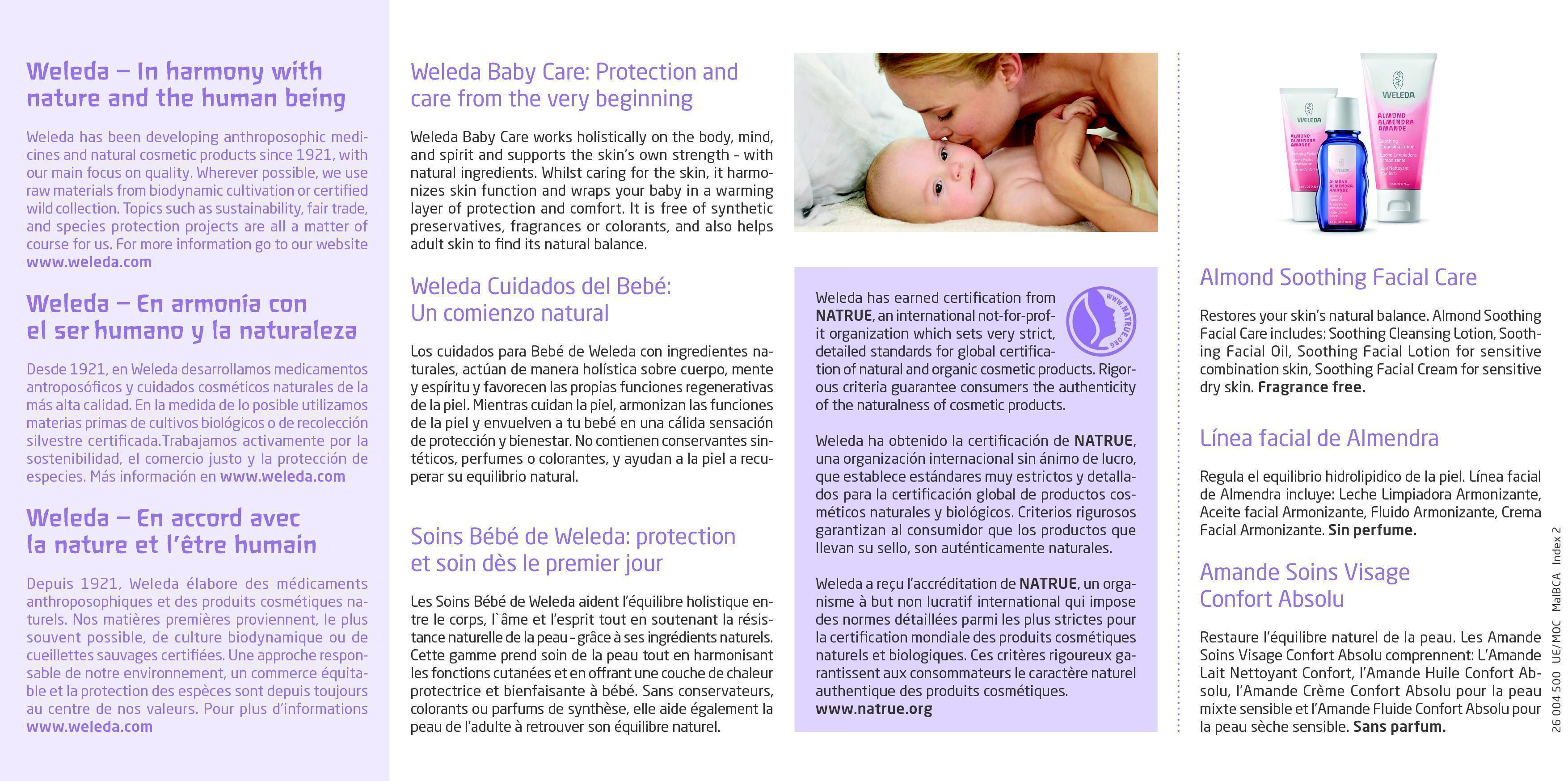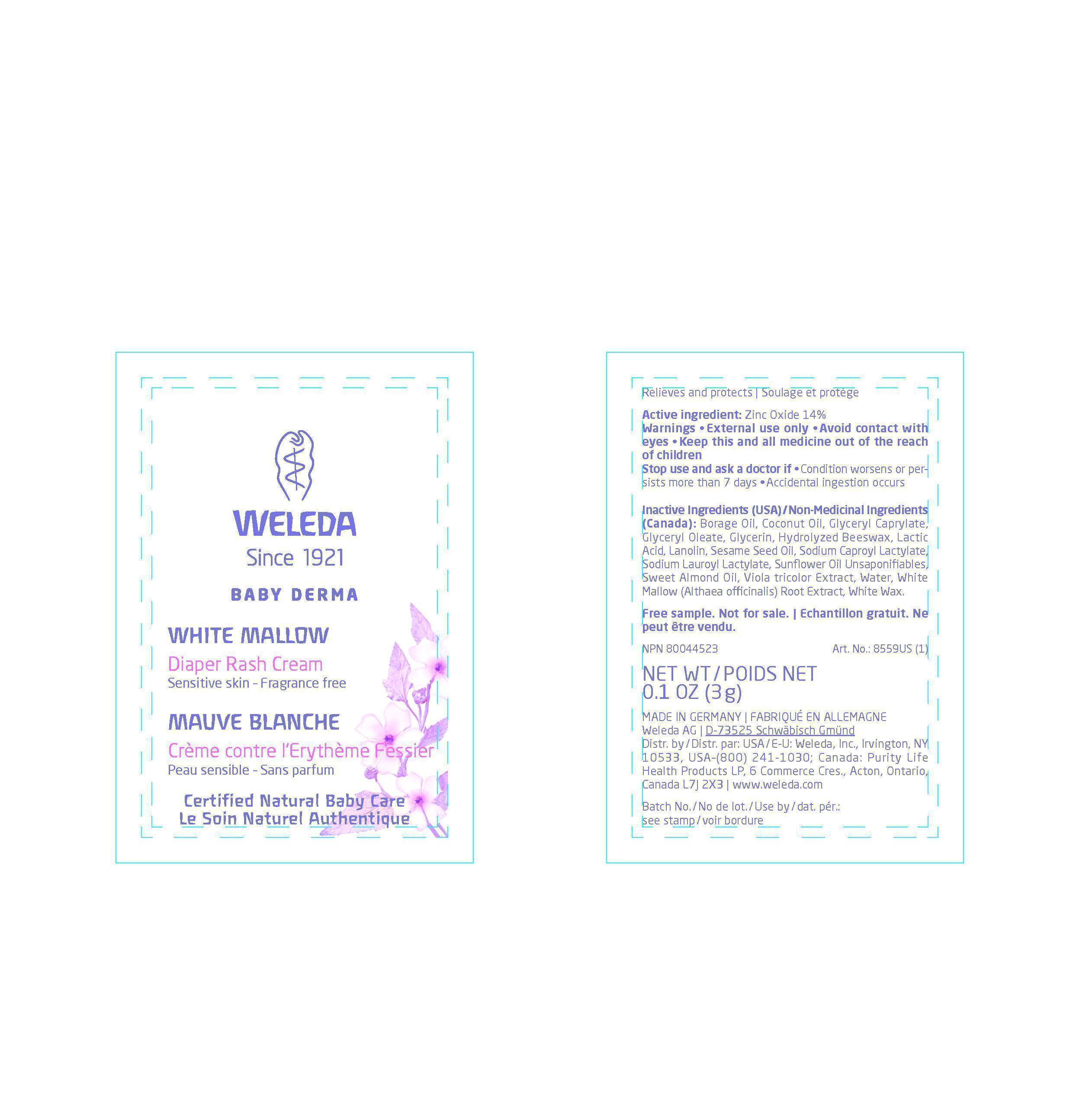 DRUG LABEL: WHITE MALLOW DIAPER RASH CREAM
NDC: 55946-702 | Form: CREAM
Manufacturer: Weleda, Inc.
Category: otc | Type: HUMAN OTC DRUG LABEL
Date: 20140826

ACTIVE INGREDIENTS: ZINC OXIDE 14 g/100 g
INACTIVE INGREDIENTS: BORAGE OIL; COCONUT OIL; GLYCERYL CAPRYLATE; GLYCERYL OLEATE; GLYCERIN; YELLOW WAX; LACTIC ACID; LANOLIN; SESAME OIL; SODIUM CAPROYL LACTYLATE; SODIUM LAUROYL LACTYLATE; SUNFLOWER OIL; ALMOND OIL; VIOLA TRICOLOR; WATER; ALTHAEA OFFICINALIS ROOT; WHITE WAX

WHITE MALLOW DIAPER RASH CREAM

PACKAGE LABEL

Weleda

Since 1921

Baby Derma

White Mallow

Diaper Rash Cream

Relieves and protects

Sensitive Skin - Fragrance free

Mauve Blanche

Crème contre l`Erythème Fessier

Soulage et protège

Peau sensible - Sans parfum

Certified Natural Baby Care

Le Soin Naturel Authentique

NPN 80044523

NET WT / POIDS NET 1.9 OZ (55.1g)

Active ingredient

Zinc Oxide 14%

Purpose

Diaper Rash Cream

KEEP OUT OF REACH OF CHILDREN

Keep this and all medicines out of the reach of children.

Uses

Temporarily helps to relieve minor skin irritations due to diaper rash.

Protects chafed skin from minor skin irritations, for sensitive skin.

Helps protect from wetness that causes diaper rash.

Warnings

External use only.

Avoid contact with eyes.

Keep this and all medicines out of the reach of children.

Directions

Cleanse area, pat dry, then apply a thin layer of cream.

Use after each diaper change until skin irritation heals, or as directed by a physician.

Inactive Ingredients (USA) / Non-Medicinal Ingredients (Canada):

Borage Oil, Coconut Oil, Glyceryl Caprylate, Glyceryl Oleate, Glycerin, Hydrolyzed Beeswax, Lactic Acid, Lanolin, Sesame Seed Oil, Sodium Caproyl Lactylate, Sodium Lauroyl Lactylate, Sunflower Oil Unsaponifiables, Sweet Almond Oil, Viola tricolor Extract, Water, White Mallow (Althaea officinalis) Root Extract, White Wax.

PACKAGE LABEL

Weleda

Since 1921

Baby Derma

White Mallow

Diaper Rash Cream

Sensitive Skin - Fragrance free

Mauve Blanche

Crème contre l'Erythème Fessier

Peau sensible - Sans parfum

Certified Natural Baby Care

Le Soin Naturel Authentique

NET WT / POIDS NET 0.1 OZ (3g)